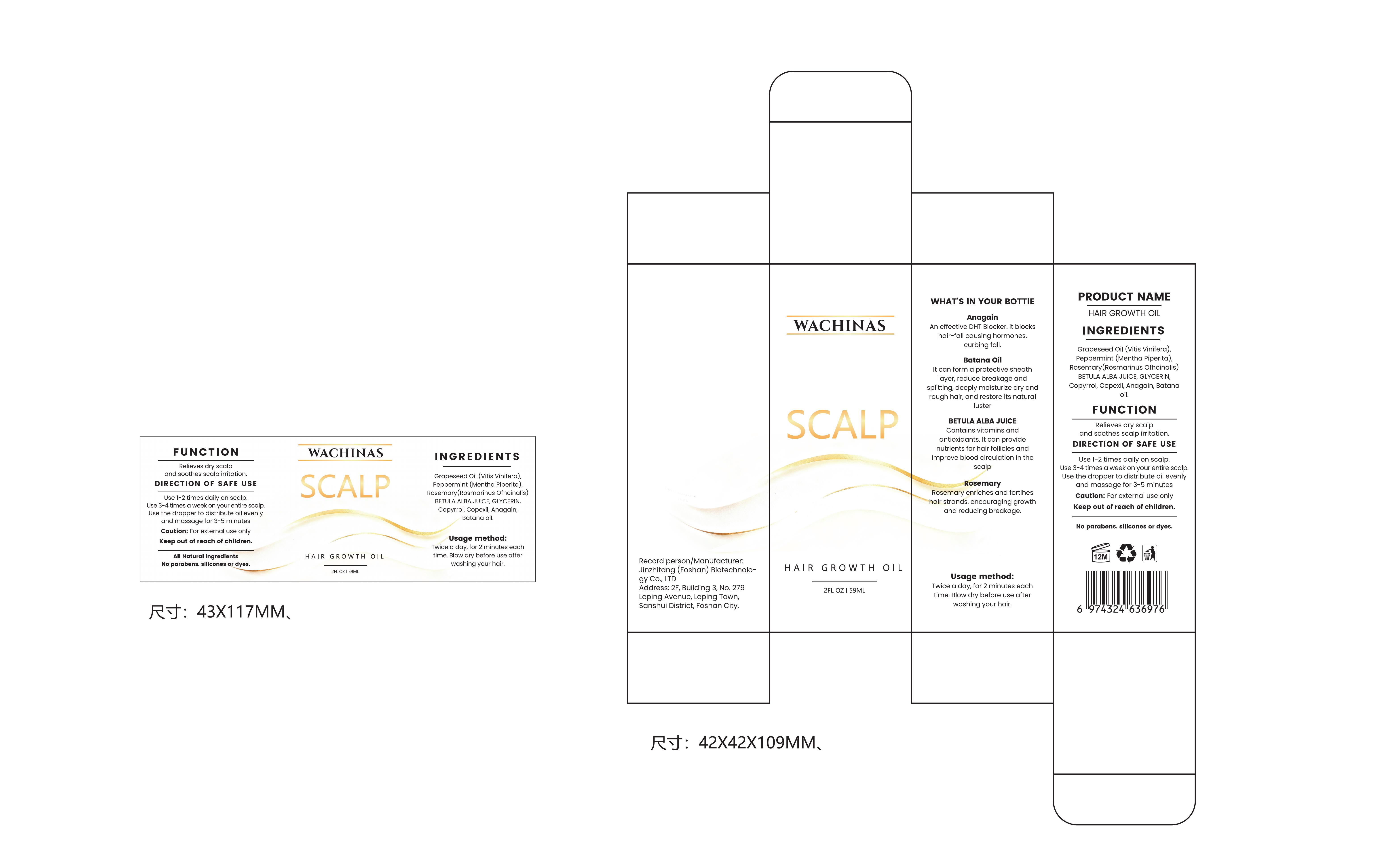 DRUG LABEL: WACHINAS Hair Growth Oil
NDC: 87104-0101 | Form: OIL
Manufacturer: Jinzhitang (Foshan) Biotechnology Co.,LTD
Category: otc | Type: HUMAN OTC DRUG LABEL
Date: 20251115

ACTIVE INGREDIENTS: DIAMINOPYRIMIDINE OXIDE 590 mg/59 g; ROSEMARY 20 g/59 g; PYRROLIDINYL DIAMINOPYRIMIDINE OXIDE 590 mg/59 g; BETULA ALBA JUICE 5 g/59 g
INACTIVE INGREDIENTS: PEPPERMINT 20 g/59 g

WARNINGS AND PRECAUTIONS

Caution:

1. For external use only
2. Keep out of reach of children.

DOSAGE AND ADMINISTRATION

1. Twice a day, for 2 minutes eachtime, Blow dry before use afterwashing your hair.
2. Use 3-4 times a week on your entire scalp
3. Use the dropper to distribute oil evenlyand massage for 3-5 minutes

WARNINGS

For external use only

INACTIVE INGREDIENT

1. Grapeseed Oil (Vitis Vinifera)
2. Anagain
3. Batana oil

KEEP OUT OF REACH OF CHILDREN

Caution: For external use only

Keep out of reach of children.

PURPOSE

WHAT'S IN YOUR BOTTIE
Anagain

An effective DHT Blocker. it blockshair-fall causing hormones.curbing fall.
Batana oil

It can form a protective sheathlayer,reduce breakage andsplitting, deeply moisturize dry andrough hair, and restore its naturalluster
BETULA ALBA JUICE

Contains vitamins and antioxidants.lt can providenutrients for hair follicles andimprove blood circulation in the scalp
Rosemary

Rosemary enriches and fortiheshair strands. encouraging growthand reducing breakage.

Usage method:

1. Twice a day, for 2 minutes eachtime. Blow dry before use afterwashing your hair.